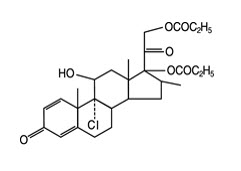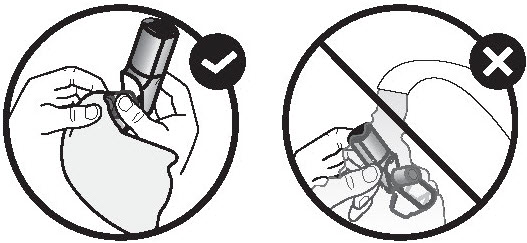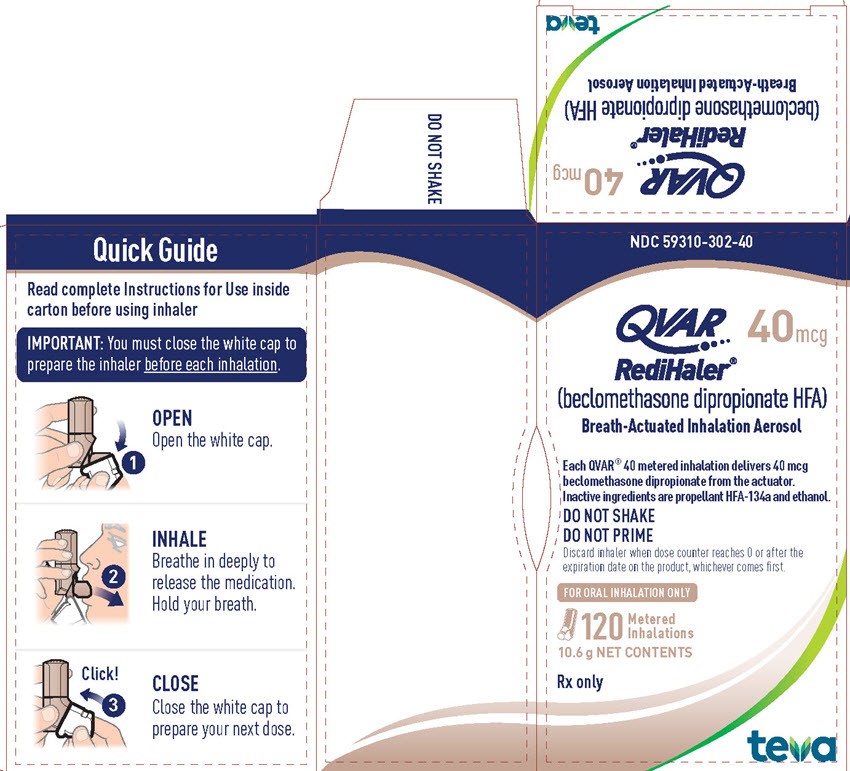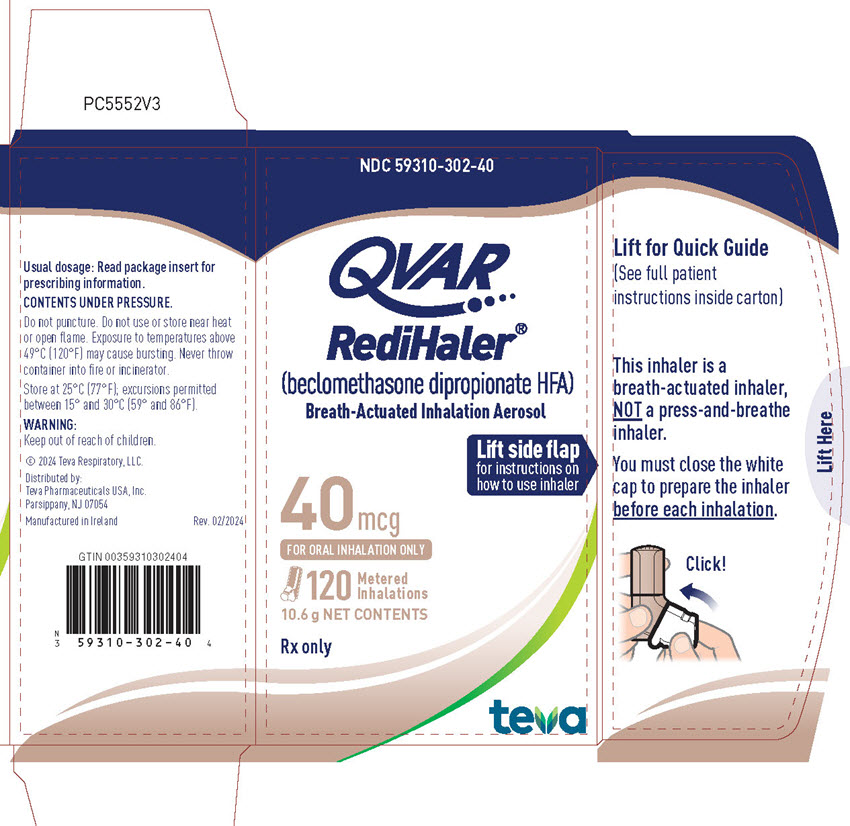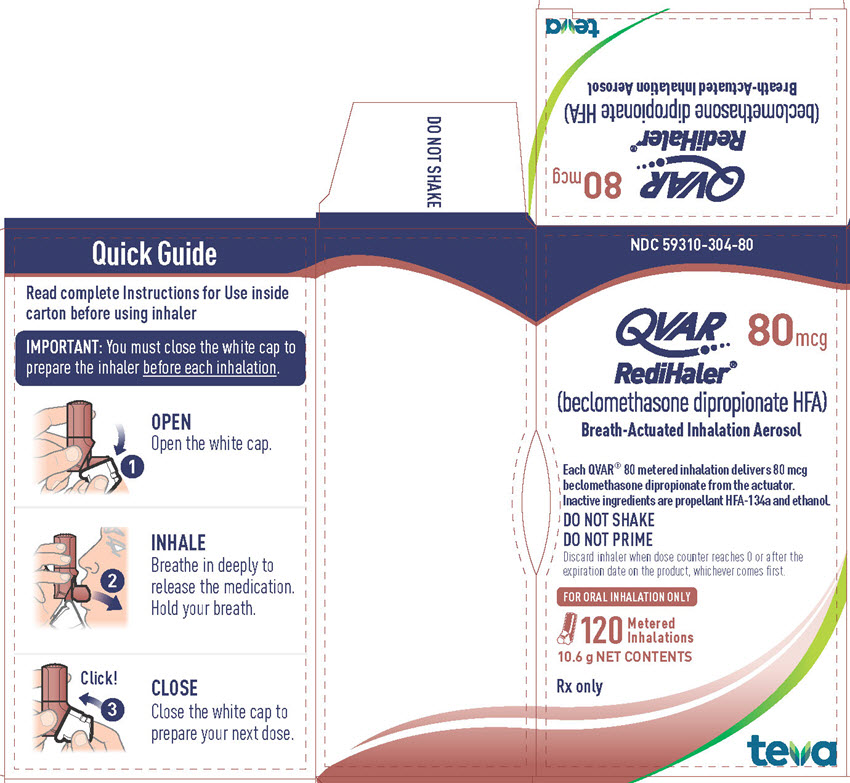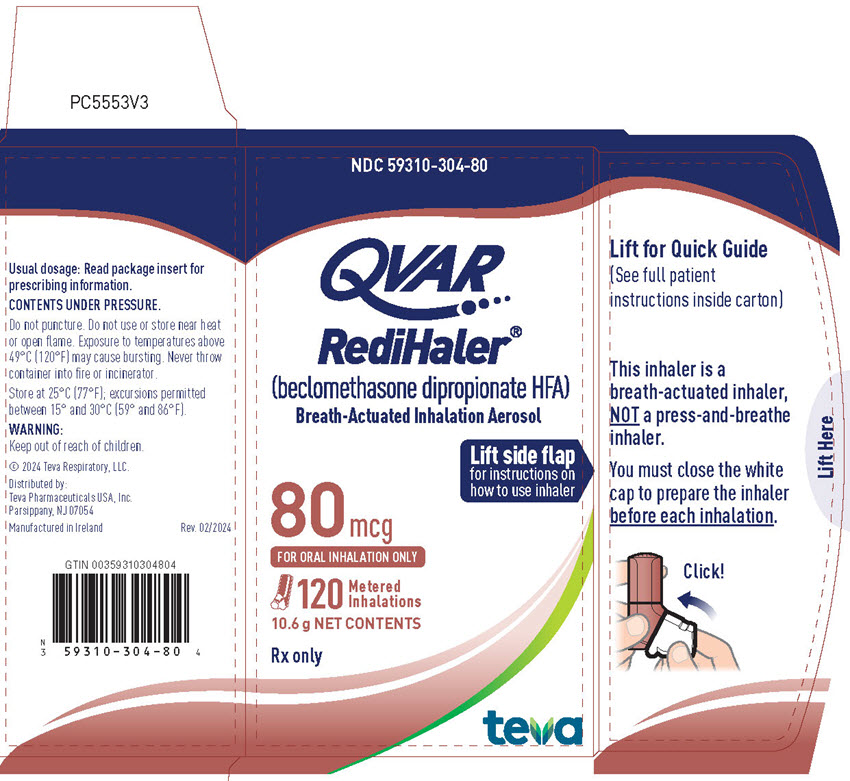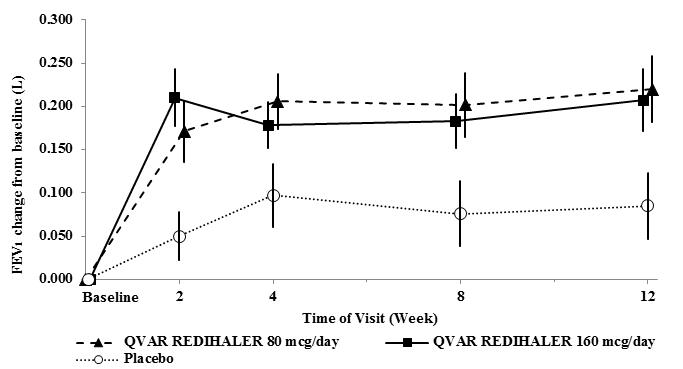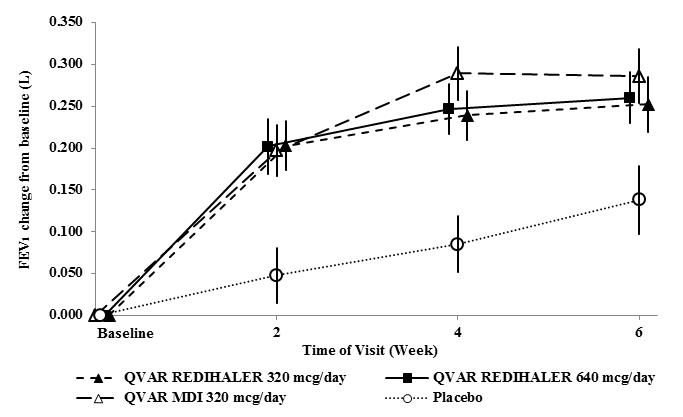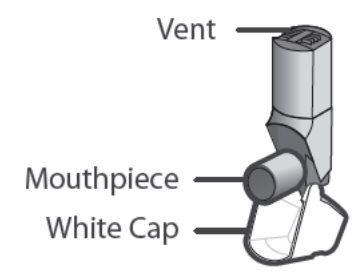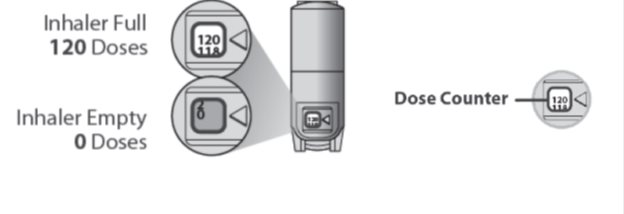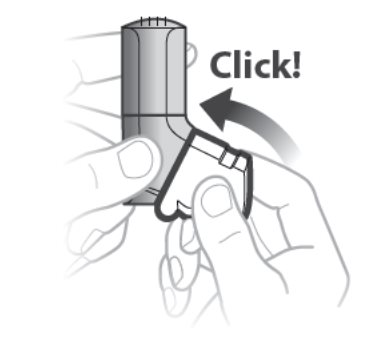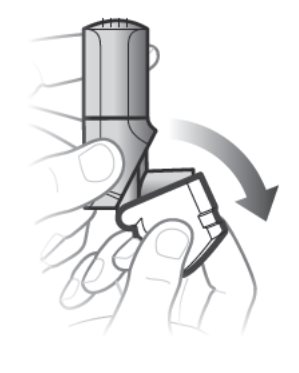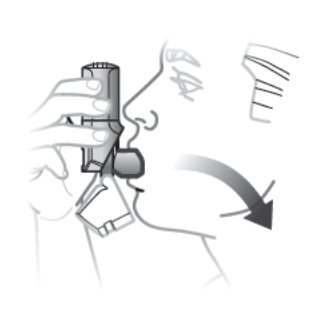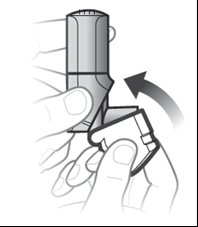 DRUG LABEL: QVAR REDIHALER
NDC: 59310-302 | Form: AEROSOL, METERED
Manufacturer: Teva Respiratory, LLC
Category: prescription | Type: HUMAN PRESCRIPTION DRUG LABEL
Date: 20250926

ACTIVE INGREDIENTS: BECLOMETHASONE DIPROPIONATE 40 ug/1 1
INACTIVE INGREDIENTS: NORFLURANE; ALCOHOL

HIGHLIGHTS OF PRESCRIBING INFORMATION

These highlights do not include all the information needed to use QVAR REDIHALER safely and effectively. See full prescribing information for QVAR REDIHALER.
QVAR REDIHALER® (beclomethasone dipropionate HFA) inhalation aerosol, for oral inhalation use
Initial U.S. Approval: 1976

1 INDICATIONS AND USAGE

QVAR REDIHALER is a corticosteroid indicated for maintenance treatment of asthma as prophylactic therapy in adults and pediatric patients 4 years of age and older. (1)

Limitations of Use:

Not indicated for the relief of acute bronchospasm. (1)

2 DOSAGE AND ADMINISTRATION

For oral inhalation only. (2.1)

- Starting dosage is based on prior asthma therapy and disease severity. (2.2)
- Treatment of asthma in patients 4 to 11 years of age: 40 mcg or 80 mcg twice daily. (2.2)
- Treatment of asthma in patients 12 years of age and older: 40 mcg, 80 mcg, 160 mcg, or 320 mcg twice daily (2.2)
- Discard QVAR REDIHALER inhaler when the dose counter displays 0 or after the expiration date on the product, whichever comes first. (2.1)
- Do not use a spacer or volume holding chamber (2.1)

3 DOSAGE FORMS AND STRENGTHS

Inhalation aerosol: 40 mcg or 80 mcg per breath actuation. (3)

4 CONTRAINDICATIONS

- Primary treatment of status asthmaticus or other acute episodes of asthma where intensive measures are required. (4)
- Hypersensitivity to any of the ingredients of QVAR REDIHALER. (4)

5 WARNINGS AND PRECAUTIONS

- Oropharyngeal candidiasis: Candida albicans infection of the mouth and throat may occur. Monitor patients periodically for signs of adverse effects on the oral cavity. Advise patients to rinse the mouth with water without swallowing after inhalation to help reduce the risk. (5.1)
- Deterioration of asthma and acute episodes: Do not use QVAR REDIHALER for relief of acute symptoms. Patients require immediate re-evaluation during rapidly deteriorating asthma. (5.2)
- Transferring patients from systemic corticosteroids: Risk of impaired adrenal function when transferring from oral steroids. Taper patients slowly from systemic corticosteroids if transferring to QVAR REDIHALER. (5.3)
- Immunosuppression: Potential worsening of existing tuberculosis, fungal, bacterial, viral, or parasitic infection; or ocular herpes simplex infections. More serious or even fatal course of chickenpox or measles can occur in susceptible patients. Use with caution in patients with these infections because of the potential for worsening of these infections. (5.4)
- Paradoxical bronchospasm: Bronchospasm, with an immediate increase in wheezing, may occur after dosing. Treat bronchospasm immediately with inhaled, short-acting bronchodilator and discontinue QVAR REDIHALER. (5.5)
- Hypersensitivity reactions: Hypersensitivity reactions, such as urticaria, angioedema, rash, and bronchospasm may occur. Discontinue QVAR REDIHALER if such reactions occur. (5.6)
- Hypercorticism and adrenal suppression: May occur with very high dosages or at the regular dosage in susceptible individuals. If such changes occur, discontinue QVAR REDIHALER slowly. (5.7)
- Effects on growth: Monitor growth of pediatric patients. (5.8)
- Decreases in bone mineral density: Monitor patients with major risk factors for decreased bone mineral content. (5.9)
- Glaucoma and cataracts: Monitor patients with change in vision or with a history of increased intraocular pressure, blurred vision, glaucoma, and/or cataracts closely. (5.10)

6 ADVERSE REACTIONS

Most common adverse reactions (incidence >3% and > placebo) include oral candidiasis, upper respiratory tract infection, nasopharyngitis, allergic rhinitis, oropharyngeal pain and sinusitis. (6.1)

To report SUSPECTED ADVERSE REACTIONS, contact Teva Pharmaceuticals at 1-888-483-8279 or FDA at 1-800-FDA-1088 or www.fda.gov/medwatch.

FULL PRESCRIBING INFORMATION

1 INDICATIONS AND USAGE

QVAR REDIHALER is indicated in the maintenance treatment of asthma as prophylactic therapy in adults and pediatric patients 4 years of age and older.

Limitations of Use:

QVAR REDIHALER is not indicated for the relief of acute bronchospasm.

2 DOSAGE AND ADMINISTRATION

2.1 General Overview

Administration

- Administer QVAR REDIHALER by oral inhalation.

- After inhalation, rinse mouth with water without swallowing to help reduce the risk of oropharyngeal candidiasis.

- Consistent dose delivery is achieved, whether using the 40‑ or 80‑mcg strengths, due to proportionality of the 2 products (i.e., 2 actuations of 40‑mcg strength should provide a dose comparable to 1 actuation of the 80‑mcg strength).
  Inhaler Instructions
- Patients should be instructed on the proper use of their inhaler.
- Do not use QVAR REDIHALER with a spacer or volume holding chamber.
- Shaking the inhaler prior to use is not necessary. Do not shake the inhaler with the cap open to avoid possible actuation of the device.

Priming

- QVAR REDIHALER does not require priming.

Cleaning

- Keep the inhaler clean and dry at all times. Never wash or put any part of the inhaler in water. Wipe the mouthpiece weekly with a clean, dry cloth or tissue.

Dose Counter

QVAR REDIHALER has a dose counter attached to the actuator. When the patient receives the inhaler, the number 120 will be displayed. The dose counter will count down each time a spray is released. When the dose counter reaches 20, the color of the numbers will change to red to remind the patient to contact their pharmacist for a refill of medication or consult their physician for a prescription refill. When the dose counter reaches 0, the background will change to solid red. Discard QVAR REDIHALER inhaler when the dose counter displays 0 or after the expiration date on the product, whichever comes first [see Patient Counseling Information (17)].

2.2 Recommended Dosage

Adults and Adolescents 12 years of age and older

The recommended starting dosage for patients 12 years of age and older who are not on an inhaled corticosteroid is 40 to 80 mcg twice daily by oral inhalation, approximately 12 hours apart.

- The starting dosage is based on previous asthma therapy and disease severity, including consideration of the patients’ current control of asthma symptoms and risk of future exacerbation.

- For patients switching to QVAR REDIHALER from another inhaled corticosteroid product, select the appropriate starting dosage strength of QVAR REDIHALER based on the strength of the previous inhaled corticosteroid product and disease severity: 40, 80, 160 or 320 mcg twice daily.

- For patients who do not respond adequately to the initial dosage after 2 weeks of therapy, increasing the dosage may provide additional asthma control. The maximum recommended dosage for patients 12 years of age and older is 320 mcg twice daily.

Pediatric Patients 4 to 11 years

The recommended starting dosage for patients aged 4 to 11 years of age is 40 mcg twice daily by oral inhalation, approximately 12 hours apart.

- The starting dosage is based on previous asthma therapy and disease severity, including consideration of the patients’ current control of asthma symptoms and risk of future exacerbation.

- For patients who do not respond adequately to QVAR REDIHALER 40 mcg after 2 weeks of therapy, increasing the dosage to QVAR REDIHALER 80 mcg twice daily may provide additional asthma control.

- The maximum recommended dosage for patients 4 to 11 years of age is 80 mcg twice daily.

General Dosing Recommendations

The onset and degree of symptom relief will vary in individual patients. Improvement in asthma symptoms can occur within 24 hours of the beginning of treatment and should be expected within the first or second week, but maximum benefit should not be expected until 3 to 4 weeks of therapy. Improvement in pulmonary function is usually apparent within 1 to 4 weeks after the start of therapy.

If a dosage regimen of QVAR REDIHALER fails to provide adequate control of asthma, the therapeutic regimen should be re-evaluated and additional therapeutic options (e.g., replacing the current strength of QVAR REDIHALER with a higher strength, or adding additional controller therapies) should be considered.

As with any inhaled corticosteroid, physicians are advised to titrate the dose of QVAR REDIHALER downward over time to the lowest level that maintains proper asthma control. This is particularly important in children since a controlled study has shown that beclomethasone dipropionate has the potential to affect growth in children.

3 DOSAGE FORMS AND STRENGTHS

Inhalation aerosol: a pressurized, breath‑actuated, metered-dose aerosol with a dose counter in 2 strengths

- 40 mcg in an aluminum canister contained within a beige plastic actuator and a hinged white cap

- 80 mcg in an aluminum canister contained within a maroon plastic actuator and a hinged white cap

4 CONTRAINDICATIONS

QVAR REDIHALER is contraindicated in:

- the primary treatment of status asthmaticus or other acute episodes of asthma where intensive measures are required [see Warnings and Precautions (5.2)].

- in patients with known hypersensitivity to beclomethasone dipropionate or any of the ingredients in QVAR REDIHALER [see Warnings and Precautions (5.6)].

5 WARNINGS AND PRECAUTIONS

5.1 Oropharyngeal Candidiasis

Localized infections with Candida albicans have occurred in the mouth and pharynx in some patients receiving QVAR REDIHALER. If oropharyngeal candidiasis develops, it should be treated with appropriate local or systemic (i.e., oral) antifungal therapy while still continuing with QVAR REDIHALER therapy, but at times therapy with QVAR REDIHALER may need to be temporarily interrupted under close medical supervision. After inhalation, the patient should rinse his/her mouth with water without swallowing to help reduce the risk of oropharyngeal candidiasis.

5.2 Deterioration of Asthma and Acute Episodes

QVAR REDIHALER is not indicated for the relief of acute symptoms, i.e., as rescue therapy for the treatment of acute episodes of bronchospasm. An inhaled, short‑acting beta2‑agonist, not QVAR REDIHALER, should be used to relieve acute symptoms such as shortness of breath. Instruct patients to contact their physician immediately if episodes of asthma that are not responsive to bronchodilators occur during the course of treatment with QVAR REDIHALER. During such episodes, patients may require therapy with oral corticosteroids.

5.3 Transferring Patients from Systemic Corticosteroid Therapy

HPA Suppression/Adrenal Insufficiency

Particular care is needed in patients who are transferred from systemically active corticosteroids to QVAR REDIHALER because deaths due to adrenal insufficiency have occurred in asthmatic patients during and after transfer from systemic corticosteroids to less systemically available inhaled corticosteroids. After withdrawal from systemic corticosteroids, a number of months are required for recovery of hypothalamic‑pituitary‑adrenal (HPA) function.

Patients who have been previously maintained on 20 mg or more per day of prednisone (or its equivalent) may be most susceptible, particularly when their systemic corticosteroids have been almost completely withdrawn. During this period of HPA suppression, patients may exhibit signs and symptoms of adrenal insufficiency when exposed to trauma, surgery, or infections (particularly gastroenteritis) or other conditions with severe electrolyte loss. Although QVAR REDIHALER may provide control of asthmatic symptoms during these episodes, in recommended doses it supplies less than normal physiological amounts of glucocorticoid systemically and does NOT provide the mineralocorticoid that is necessary for coping with these emergencies.

During periods of stress or a severe asthmatic attack, patients who have been withdrawn from systemic corticosteroids should be instructed to resume oral corticosteroids (in large doses) immediately and to contact their physician for further instruction. These patients should also be instructed to carry a warning card indicating that they may need supplementary systemic steroids during periods of stress or a severe asthma attack.

Patients requiring oral or other systemic corticosteroids should be weaned slowly from oral or other systemic corticosteroid use after transferring to QVAR REDIHALER. Lung function (FEV1 or PEF), beta‑agonist use, and asthma symptoms should be carefully monitored during withdrawal of oral or other systemic corticosteroids. In addition to monitoring asthma signs and symptoms, patients should be observed for signs and symptoms of adrenal insufficiency such as fatigue, lassitude, weakness, nausea and vomiting, and hypotension.

Unmasking of Allergic Conditions Previously Suppressed by Systemic Corticosteroids

Transfer of patients from systemic corticosteroid therapy to QVAR REDIHALER may unmask allergic conditions previously suppressed by the systemic corticosteroid therapy, e.g., rhinitis, conjunctivitis, eczema, arthritis, and eosinophilic conditions.

Corticosteroid Withdrawal Symptoms

During withdrawal from oral corticosteroids, some patients may experience symptoms of systemically active corticosteroid withdrawal, e.g., joint and/or muscular pain, lassitude, and depression, despite maintenance or even improvement of respiratory function.

5.4 Immunosuppression and Risk of Infections

Persons who are on drugs which suppress the immune system are more susceptible to infections than healthy individuals. Chickenpox and measles, for example, can have a more serious or even fatal course in non-immune patients on corticosteroids. In such patients who have not had these diseases or been properly immunized, particular care should be taken to avoid exposure. It is not known how the dose, route and duration of corticosteroid administration affect the risk of developing a disseminated infection, and nor is the contribution of the underlying disease and/or prior corticosteroid treatment known. If exposed to chickenpox, prophylaxis with varicella-zoster immune globulin (VZIG) may be indicated. If exposed to measles, prophylaxis with pooled intramuscular immunoglobulin (IG) may be indicated (See the respective package inserts for complete VZIG and IG prescribing information.) If chickenpox develops, treatment with antiviral agents may be considered.

Inhaled corticosteroids should be used with caution, if at all, in patients with active or quiescent tuberculosis infection of the respiratory tract; untreated systemic fungal, bacterial, parasitic or viral infections; or ocular herpes simplex.

5.5 Paradoxical Bronchospasm

Inhaled corticosteroids may produce inhalation‑induced bronchospasm with an immediate increase in wheezing after dosing that may be life-threatening. If inhalation induced bronchospasm occurs following dosing with QVAR REDIHALER, it should be treated immediately with an inhaled, short‑acting bronchodilator. Treatment with QVAR REDIHALER should be discontinued and alternate therapy instituted.

5.6 Immediate Hypersensitivity Reactions

Hypersensitivity reactions, such as urticaria, angioedema, rash, and bronchospasm, may occur after administration of QVAR REDIHALER. Discontinue QVAR REDIHALER if such reactions occur [see Contraindications (4)].

5.7 Hypercorticism and Adrenal Suppression

QVAR REDIHALER will often help control asthma symptoms with less suppression of HPA function than therapeutically equivalent oral doses of prednisone. Since beclomethasone dipropionate is absorbed into the circulation and can be systemically active at higher doses, the beneficial effects of QVAR REDIHALER in minimizing HPA dysfunction may be expected only when recommended dosages are not exceeded and individual patients are titrated to the lowest effective dose.

Because of the possibility of systemic absorption of inhaled corticosteroids, patients treated with QVAR REDIHALER should be observed carefully for any evidence of systemic corticosteroid effects. Particular care should be taken in observing patients postoperatively or during periods of stress for evidence of inadequate adrenal response.

It is possible that systemic corticosteroid effects such as hypercorticism and adrenal suppression (including adrenal crisis) may appear in a small number of patients, particularly when beclomethasone dipropionate is administered at higher than recommended doses over prolonged periods of time. If such effects occur, the dosage of QVAR REDIHALER should be reduced slowly, consistent with accepted procedures for reducing systemic corticosteroids and for management of asthma symptoms.

5.8 Effects on Growth

Orally inhaled corticosteroids, including QVAR REDIHALER, may cause a reduction in growth velocity when administered to pediatric patients. Monitor the growth of pediatric patients receiving QVAR REDIHALER routinely (e.g., via stadiometry). To minimize the systemic effects of orally inhaled corticosteroids, including QVAR REDIHALER, titrate each patient’s dose to the lowest dosage that effectively controls his/her symptoms [see Use in Specific Populations (8.4)].

5.9 Reduction in Bone Mineral Density

Decreases in bone mineral density (BMD) have been observed with long‑term administration of products containing inhaled corticosteroids. The clinical significance of small changes in BMD with regard to long‑term outcomes, such as fracture, is unknown. Patients with major risk factors for decreased bone mineral content, such as prolonged immobilization, family history of osteoporosis, or chronic use of drugs that can reduce bone mass (e.g., anticonvulsants and corticosteroids) should be monitored and treated with established standards of care.

5.10 Glaucoma and Cataracts

Glaucoma, increased intraocular pressure, blurred vision and cataracts have been reported following the use of long-term administration of inhaled corticosteroids. Therefore, close monitoring is warranted in patients with a change in vision or with a history of increased intraocular pressure, blurred vision, glaucoma, and/or cataracts while using QVAR REDIHALER.

6 ADVERSE REACTIONS

The following clinically significant adverse reactions are described elsewhere in the labeling:

- Oropharyngeal candidiasis [see Warnings and Precautions (5.1)]

- Immunosuppression and risk of infections [see Warnings and Precautions (5.4)]

- Hypercorticism and adrenal suppression [see Warnings and Precautions (5.7)]

- Reduction in bone mineral density [see Warnings and Precautions (5.9)]

- Growth effects [see Warnings and Precautions (5.8) and Use in Specific Populations (8.4)]

- Glaucoma and cataracts [see Warnings and Precautions (5.10)]

6.1 Clinical Trials Experience

A total of 1858 subjects participated in the QVAR REDIHALER clinical development program. Because clinical trials are conducted under widely varying conditions, adverse reaction rates observed in the clinical trials of a drug cannot be directly compared to rates in the clinical trials of another drug and may not reflect the rates observed in practice.

Adults and Adolescent Patients 12 years of Age and Older: The adverse reaction information presented in Table 1 is derived from 3 double-blind, placebo-controlled clinical trials in which 1230 patients (751 female and 479 male adults previously treated with as‑needed bronchodilators and/or inhaled corticosteroids) were treated with QVAR REDIHALER (doses of 40, 80, 160, or 320 mcg twice daily) or QVAR (beclomethasone dipropionate HFA) Inhalation Aerosol (QVAR MDI; doses of 160 or 320 mcg twice daily) or placebo. In considering these data, difference in average duration of exposure and clinical trial design should be taken into account.

Table 1: Adverse Reactions Experienced by at Least 3% of Adult and Adolescent Patients in the QVAR REDIHALER or QVAR MDI Groups and Greater Than Placebo by Treatment and Daily Dose

Preferred; Term | Number (%) of patients
 | QVAR REDIHALER |  |  |  | QVAR MDI |  | Placebo
 | 80 mcg; N=90 | 160 mcg; N=92 | 320 mcg; N=214 | 640 mcg; N=211 | 320 mcg; N=212 | 640 mcg; N=107 | N=304
Oral Candidiasis | 0 | 2 (2) | 7 (3) | 15 (7) | 6 (3) | 9 (8) | 1 (<1)
Upper Respiratory Tract Infection | 3 (3) | 3 (3) | 9 (4) | 6 (3) | 17 (8) | 4 (4) | 6 (2)
Nasopharyngitis | 4 (4) | 2 (2) | 3 (1) | 3 (1) | 6 (3) | 4 (4) | 4 (1)
Oropharyngeal Pain | 2 (2) | 2 (2) | 1 (<1) | 3 (1) | 6 (3) | 4 (4) | 2 (<1)
Viral Upper Respiratory Tract Infection | 3 (3) | 0 | 1 (<1) | 3 (1) | 4 (2) | 2 (<1) | 4 (1)
Sinusitis | 3 (3) | 0 | 1 (<1) | 2 (<1) | 1 (<1) | 1 (<1) | 2 (<1)
Rhinitis Allergic | 0 | 3 (3) | 0 | 2 (<1) | 0 | 1 (<1) | 0

*QVAR MDI=QVAR Inhalation Aerosol

Other adverse reactions that occurred in clinical trials using QVAR REDIHALER with an incidence of 1% to 3% and which occurred at a greater incidence than placebo were back pain, headache, pain, nausea and cough.

Pediatric Patients 4 to 11 Years of Age: The adverse reaction information presented in Table 2 concerning QVAR REDIHALER and QVAR MDI is derived from one 12‑week placebo-controlled study in pediatric patients 4 to 11 years of age with persistent asthma.

Table 2: Adverse Reactions Experienced by at Least 3% of Patients 4 to 11 Years of Age in the QVAR REDIHALER or QVAR MDI Groups and Greater Than Placebo by Treatment and Daily Dose

Preferred Term | Number (%) of patients
 | QVAR REDIHALER |  | QVAR MDI |  | Placebo
 | 80 mcg; N=126 | 160 mcg N=125 | 80 mcg; N=125 | 160 mcg; N=125 | N=127
Upper Respiratory Tract Infection | 3 (2.4) | 1 (0.8) | 6 (4.8) | 5 (4.0) | 5 (3.9)
Nasopharyngitis | 5 (4.0) | 11 (8.8) | 6 (4.8) | 6 (4.8) | 4 (3.1)
Viral Upper Respiratory Tract Infection | 5 (4.0) | 5 (4.0) | 3 (2.4) | 1 (0.8) | 4 (3.1)
Pharyngitis | 4 (3.2) | 4 (3.2) | 4 (3.2) | 4 (3.2) | 2 (1.6)
Cough | 1 (0.8) | 3 (2.4) | 9 (7.2) | 6 (4.8) | 4 (3.1)
Vomiting | 2 (1.6) | 2 (1.6) | 4 (3.2) | 0 | 2 (1.6)
Headache | 2 (1.6) | 5 (4.0) | 0 | 4 (3.2) | 5 (3.9)
Pyrexia | 1 (0.8) | 4 (3.2) | 4 (3.2) | 3 (2.4) | 3 (2.4)

*QVAR MDI=QVAR Inhalation Aerosol

Other adverse reactions that occurred in clinical trials using QVAR REDIHALER with an incidence of 1% to 3% and which occurred at a greater incidence than placebo were influenza, gastroenteritis viral, ear infection, oral candidiasis, diarrhea, and myalgia.

6.2 Postmarketing Experience

In addition to the adverse reactions reported from clinical trials with QVAR REDIHALER, the following adverse reactions have been identified during post-approval use of QVAR MDI and other inhaled corticosteroids. Because these reactions are reported voluntarily from a population of uncertain size, it is not always possible to reliably estimate their frequency or establish a causal relationship to drug exposure.

Local Effects: Localized infections with Candida albicans have occurred in patients treated with beclomethasone dipropionate or other orally inhaled corticosteroids [see Warnings and Precautions (5.1)].

Psychiatric and Behavioral Changes: Aggression, depression, sleep disorders, psychomotor hyperactivity, and suicidal ideation have been reported (primarily in children).

Eye Disorders: Blurred vision, central serous chorioretinopathy (CSC).

8 USE IN SPECIFIC POPULATIONS

8.1 Pregnancy

Risk Summary

There are no adequate and well‑controlled studies with QVAR REDIHALER or beclomethasone dipropionate in pregnant women. There are clinical considerations with the use of inhaled corticosteroids (ICS), including beclomethasone dipropionate, in pregnant women [see Clinical Considerations]. Also, no published studies, including studies of large birth registries, have to date related the use of ICS to any increases in congenital malformations or other adverse perinatal outcomes. Thus, available human data do not establish the presence or absence of drug‑associated risk to the fetus. In animal reproduction studies, beclomethasone dipropionate resulted in adverse developmental effects in mice and rabbits at subcutaneous doses equal to or greater than approximately 0.75 times the maximum recommended human daily inhalation dose (MRHDID) in adults (0.64 mg/day) [see Data]. In rats exposed to beclomethasone dipropionate by inhalation, dose‑related gross injury to the fetal adrenal glands was observed at doses greater than 180 times the MRHDID, but there was no evidence of external or skeletal malformations or embryolethality at inhalation doses of up to 440 times the MRHDID.

The estimated background risk of major birth defects and miscarriage for the indicated population(s) are unknown. In the US general population, the estimated risk of major birth defects and miscarriage in clinically recognized pregnancies is 2‑4% and 15‑20%, respectively.

Clinical Considerations

Disease-Associated Maternal and/or Embryo/Fetal Risk

The risk of complications to the mother and developing fetus from inadequate control of asthma must be balanced against the risks from exposure to beclomethasone dipropionate. In women with poorly or moderately controlled asthma, evidence demonstrates that there is an increased risk of preeclampsia in the mother and prematurity, low birth weight, and small for gestational age for the neonate. The level of asthma control should be closely monitored in pregnant women and treatment adjusted to maintain optimal control.

Labor or Delivery

There are no specific human data regarding any adverse effects of inhaled beclomethasone dipropionate on labor and delivery.

Data

Animal Data

In an embryofetal development study in pregnant rats, beclomethasone dipropionate administration during organogenesis from gestation days 6 to 15 at inhaled doses 180 times the MRHDID in adults and higher (on a mg/m^2 basis at maternal doses of 11.5 and 28.3 mg/kg/day) produced dose‑dependent gross injury (characterized by red foci) of the adrenal glands in fetuses. There were no findings in the adrenal glands of rat fetuses at an inhaled dose that was 40 times the MRHDID in adults (on a mg/m^2 basis at a maternal dose of 2.4 mg/kg/day). There was no evidence of external or skeletal malformations or embryolethality in rat at inhaled doses up to 440 times the MRHDID (on a mg/m^2 basis at maternal doses up to 28.3 mg/kg/day).

In an embryofetal development study in pregnant mice, beclomethasone dipropionate administration from gestation days 1 to 18 at subcutaneous doses equal to and greater than 0.75 times the MRHDID in adults (on a mg/m^2 basis at maternal doses of 0.1 mg/kg/day and higher) produced adverse developmental effects (increased incidence of cleft palate). A no-effect dose in mice was not identified. In a second embryofetal development study in pregnant mice, beclomethasone dipropionate administration from gestation days 1 to 13 at subcutaneous doses equal to and greater than 2.3 times the MRHDID in adults (on a mg/m^2 basis at a maternal dose of 0.3 mg/kg/day) produced embryolethal effects (increased fetal resorptions) and decreased pup survival.

In an embryofetal development study in pregnant rabbits, beclomethasone dipropionate administration during organogenesis from gestation days 7 to 16 at subcutaneous doses equal to and greater than 0.75 times the MRHDID in adults (on a mg/m^2 basis at maternal doses of 0.025 mg/kg/day and higher) produced external and skeletal malformations and embryolethal effects (increased fetal resorptions). There were no effects in fetuses of pregnant rabbits administered a subcutaneous dose 0.2 times the MRHDID in adults (on a mg/m^2 basis at a maternal dose of 0.006 mg/kg/day).

8.2 Lactation

Risk Summary

There are no data available on the presence of beclomethasone dipropionate in human milk, the effects on the breastfed child, or the effects on milk production. However, other inhaled corticosteroids have been detected in human milk. The developmental and health benefits of breastfeeding should be considered along with the mother’s clinical need for QVAR REDIHALER and any potential adverse effects on the breastfed child from beclomethasone dipropionate or from the underlying maternal condition.

8.3 Females and Males of Reproductive Potential

Impairment of fertility was observed in rats and dogs at oral doses of beclomethasone dipropionate corresponding to 250 and 25 times the MRHDID for adults on a mg/m^2 basis, respectively. [see Nonclinical Toxicology (13.1)].

8.4 Pediatric Use

The safety and effectiveness of QVAR REDIHALER for the maintenance treatment of asthma as prophylactic therapy have been established in pediatric patients aged 4 years and older. Use of QVAR REDIHALER for this indication is supported by evidence from adequate and well-controlled studies. Five-hundred and one children between the ages of 4 and 11 were treated with at least one dose of QVAR REDIHALER or QVAR MDI in one 12‑week clinical trial. The safety and effectiveness of QVAR REDIHALER in children below 4 years of age have not been established.

Controlled clinical studies have shown that inhaled corticosteroids may cause a reduction in growth velocity in pediatric patients. A 12‑month, randomized, controlled clinical trial evaluated the effects of QVAR MDI versus beclomethasone dipropionate in a CFC propellant‑based formulation (CFC‑BDP) on growth in children age 5 to 11. A total of 520 patients were enrolled, of whom 394 received QVAR MDI (100 to 400 mcg/day ex‑valve) and 126 received CFC‑BDP (200 to 800 mcg/day ex‑valve). Similar control of asthma was noted in each treatment arm. When comparing results at month 12 to baseline, the mean growth velocity in children treated with QVAR MDI was approximately 0.5 cm/year less than that noted with children treated with CFC‑BDP via large‑volume spacer. The long‑term effects of the reduction in growth velocity associated with orally inhaled corticosteroids, including the impact on final adult height, are unknown. The potential for "catch‑up" growth following discontinuation of treatment with orally inhaled corticosteroids has not been adequately studied.

The growth of children and adolescents receiving orally inhaled corticosteroids, including QVAR REDIHALER, should be monitored routinely (e.g., via stadiometry). If a child or adolescent on any corticosteroid appears to have growth suppression, the possibility that he/she is particularly sensitive to this effect should be considered. The potential growth effects of prolonged treatment should be weighed against clinical benefits obtained and the risks associated with alternative therapies. To minimize the systemic effects of orally inhaled corticosteroids, including QVAR REDIHALER, each patient should be titrated to his/her lowest effective dose [see Dosage and Administration (2.2)].

8.5 Geriatric Use

Clinical studies of QVAR REDIHALER did not include sufficient numbers of patients aged 65 and over to determine whether they respond differently from younger patients. Other reported clinical experience has not identified differences in responses between the elderly and younger patients. In general, dose selection for an elderly patient should be cautious, usually starting at the low end of the dosing range, reflecting the greater frequency of decreased hepatic, renal, or cardiac function, and of concomitant disease or other drug therapy.

11 DESCRIPTION

The active component of QVAR REDIHALER 40 mcg Inhalation Aerosol and QVAR REDIHALER 80 mcg Inhalation Aerosol is beclomethasone dipropionate, USP, a corticosteroid having the chemical name 9-chloro-11ß,17,21-trihydroxy-16ß-methylpregna-1,4-diene-3,20-dione 17,21-dipropionate. Beclomethasone dipropionate is a diester of beclomethasone, a synthetic corticosteroid chemically related to dexamethasone. Beclomethasone differs from dexamethasone in having a chlorine at the 9‑alpha carbon in place of a fluorine, and in having a 16‑beta-methyl group instead of a 16‑alpha-methyl group. Beclomethasone dipropionate is a white to creamy white, odorless powder with a molecular formula of C28H37ClO7 and a molecular weight of 521.1. Its chemical structure is:

QVAR REDIHALER is a pressurized, breath‑actuated, metered‑dose aerosol with a dose counter intended for oral inhalation only. Each unit consists of a sealed breath‑actuated inhaler device enclosing a canister containing a solution of beclomethasone dipropionate in propellant HFA‑134a (1,1,1,2 tetrafluoroethane) and ethanol (0.85 g). QVAR REDIHALER 40 mcg delivers 40 mcg of beclomethasone dipropionate from the actuator mouthpiece and 50 mcg from the canister valve. QVAR REDIHALER 80 mcg delivers 80 mcg of beclomethasone dipropionate from the actuator mouthpiece and 100 mcg from the canister valve. Both products deliver 50 microliters (59 milligrams) of solution formulation as an aerosol from the canister valve with each actuation. The 40‑mcg canisters and the 80‑mcg canisters provide 120 inhalations each. Since the QVAR REDIHALER canister is fitted with a primeless valve, no priming actuations are required before use. For both products, an actuation was always triggered by a 20 L/min inspiratory flow rate.

12 CLINICAL PHARMACOLOGY

12.1 Mechanism of Action

Beclomethasone dipropionate is a corticosteroid demonstrating potent anti‑inflammatory activity. The precise mechanism of corticosteroid action on asthma is not known. Corticosteroids have been shown to have multiple anti‑inflammatory effects, inhibiting both inflammatory cells (e.g., mast cells, eosinophils, basophils, lymphocytes, macrophages, and neutrophils) and release of inflammatory mediators (e.g., histamine, eicosanoids, leukotrienes, and cytokines). These anti‑inflammatory actions of corticosteroids contribute to their efficacy in asthma.

Beclomethasone dipropionate is a prodrug that is rapidly activated by hydrolysis to the active monoester, 17‑monopropionate (17‑BMP). Beclomethasone‑17‑monopropionate has been shown in vitro to exhibit a binding affinity for the human glucocorticoid receptor which is approximately 13 times that of dexamethasone, 6 times that of triamcinolone acetonide, 1.5 times that of budesonide and 25 times that of beclomethasone dipropionate. The clinical significance of these findings is unknown.

Studies in patients with asthma have shown a favorable ratio between topical anti‑inflammatory activity and systemic corticosteroid effects with recommended doses of QVAR REDIHALER.

12.2 Pharmacodynamics

HPA Axis Effects

The effects of QVAR MDI on the hypothalamic‑pituitary‑adrenal (HPA) axis were studied in 40 corticosteroid-naive patients. QVAR MDI, at doses of 80, 160, or 320 mcg twice daily, was compared with placebo and 336 mcg twice daily of CFC‑BDP. Active treatment groups showed an expected dose‑related reduction in 24‑hour urinary-free cortisol (a sensitive marker of adrenal production of cortisol). Patients treated with the highest dose recommended of QVAR MDI (320 mcg twice daily) had a 37.3% reduction in 24‑hour urinary‑free cortisol compared to a reduction of 47.3% produced by treatment with 336 mcg twice daily of CFC‑BDP. There was a 12.2% reduction in 24‑hour urinary‑free cortisol seen in the group of patients that received 80 mcg twice daily of QVAR MDI and a 24.6% reduction in the group of patients that received 160 mcg twice daily. An open label study of 354 asthma patients given QVAR MDI at recommended doses for one year assessed the effect of treatment with this product on the HPA axis (as measured by both morning and stimulated plasma cortisol). Less than 1% of patients treated for one year with this product had an abnormal response (peak less than 18 mcg/dL) to a short-cosyntropin test.

12.3 Pharmacokinetics

Beclomethasone dipropionate undergoes rapid and extensive conversion to beclomethasone‑17‑monopropionate (17‑BMP) during absorption. The pharmacokinetics of beclomethasone dipropionate and 17‑BMP were studied in subjects given single doses.

Absorption

The mean peak plasma concentration (Cmax) of BDP was 6635 pg/mL at 2 minutes after inhalation of 320 mcg using QVAR REDIHALER (4 inhalations of the 80 mcg/inhalation strength). The mean peak plasma concentration of the major and most active metabolite, 17-BMP, was 1464 pg/mL at 10 minutes after inhalation of 320 mcg of QVAR REDIHALER.

Distribution

The in vitro protein binding for 17‑BMP was reported to be 94‑96% over the concentration range of 1000 to 5000 pg/mL. Protein binding was constant over the concentration range evaluated. There is no evidence of tissue storage of beclomethasone dipropionate or its metabolites.

Elimination

The major route of elimination of inhaled beclomethasone dipropionate appears to be via hydrolysis. More than 90% of inhaled beclomethasone dipropionate is found as 17‑BMP in the systemic circulation. The mean terminal half‑life of 17‑BMP is approximately 4 hours for QVAR REDIHALER.

Metabolism

Three major metabolites are formed via esterases:

- beclomethasone‑17‑monopropionate (17‑BMP)
- beclomethasone‑21‑monopropionate (21‑BMP)
- beclomethasone (BOH)

Lung slices metabolize beclomethasone dipropionate rapidly to 17‑BMP and more slowly to BOH. 17‑BMP is the most active metabolite.

Excretion

Irrespective of the route of administration (injection, oral or inhalation), beclomethasone dipropionate and its metabolites are mainly excreted in the feces. Less than 10% of the drug and its metabolites are excreted in the urine.

Specific Populations

No pharmacokinetic studies for QVAR REDIHALER have been conducted in neonates or elderly subjects.

Pediatric Patients: No pharmacokinetic studies for QVAR REDIHALER have been conducted in pediatric subjects aged of 4 to 17 years. However, the pharmacokinetics of 17‑BMP, including dose and strength proportionalities, is similar in children and adults using QVAR MDI, although the exposure is highly variable. In 17 children (mean age 10 years), the Cmax of 17‑BMP was 787 pg/mL at 0.6 hour after inhalation of 160 mcg (4 actuations of the 40 mcg/actuation strength of QVAR MDI). The systemic exposure to 17‑BMP from 160 mcg of QVAR MDI administered without a spacer was comparable to the systemic exposure to 17‑BMP from 336 mcg CFC‑BDP administered with a large volume spacer in 14 children (mean age 12 years). This implies that approximately twice the systemic exposure to 17‑BMP would be expected for comparable mg doses of QVAR MDI without a spacer and CFC‑BDP with a large volume spacer.

Male and Female Patients: The influence of sex on the pharmacokinetics of QVAR REDIHALER has not been studied.

Racial or Ethnic Groups: The influence of race on the pharmacokinetics of QVAR REDIHALER has not been studied.

Patients with Renal Impairment: The effect of renal impairment on the pharmacokinetics of QVAR REDIHALER has not been evaluated.

Patients with Hepatic Impairment: The effect of hepatic impairment on the pharmacokinetics of QVAR REDIHALER has not been evaluated.

Drug Interaction Studies: In vitro and in vivo drug interaction studies have not been conducted with QVAR REDIHALER.

13 NONCLINICAL TOXICOLOGY

13.1 Carcinogenesis, Mutagenesis, Impairment of Fertility

The carcinogenicity of beclomethasone dipropionate was evaluated in rats which were exposed for a total of 95 weeks, 13 weeks at inhalation doses up to 0.4 mg/kg/day and the remaining 82 weeks at combined oral and inhalation doses up to 2.4 mg/kg/day. There was no evidence of treatment‑related increases in the incidence of tumors in this study at the highest dose, which is approximately 37 and 72 times the MRHDID in adults and children, respectively, on a mg/m^2 basis.

Beclomethasone dipropionate did not induce gene mutation in bacterial cells or mammalian Chinese hamster ovary (CHO) cells in vitro. No significant clastogenic effect was seen in cultured CHO cells in vitro or in the mouse micronucleus test in vivo.

In rats, beclomethasone dipropionate caused decreased conception rates at an oral dose of 16 mg/kg/day (approximately 250 times the MRHDID in adults on a mg/m^2 basis). Impairment of fertility, as evidenced by inhibition of the estrous cycle in dogs, was observed following treatment by the oral route at a dose of 0.5 mg/kg/day (approximately 25 times the MRHDID in adults on a mg/m^2 basis). No inhibition of the estrous cycle in dogs was seen following 12 months of exposure to beclomethasone dipropionate by the inhalation route at an estimated daily dose of 0.33 mg/kg (approximately 17 times the MRHDID in adults on a mg/m^2 basis).

14 CLINICAL STUDIES

The safety and efficacy of QVAR REDIHALER were evaluated in 1,858 patients with asthma. The development program included 2 confirmatory trials of 12 weeks duration and 1 confirmatory trial of 6 weeks duration in patients 12 years of age and older, and 1 confirmatory trial of 12 weeks duration in patients 4 to 11 years of age. The efficacy of QVAR REDIHALER is based primarily on the confirmatory trials described below.

14.1 Trials in the Maintenance Treatment of Asthma

Adult and Adolescent Patients 12 Years of Age and Older

Two confirmatory clinical trials were conducted comparing QVAR REDIHALER with placebo in adult and adolescent patients with persistent asthma (Trial 1 and Trial 2).

Trial 1 (NCT02040779): This randomized, double-blind, parallel-group, placebo-controlled, 12-week, efficacy and safety trial compared QVAR REDIHALER 40 and 80 mcg given as 1 inhalation twice daily with placebo in adult and adolescent patients with persistent symptomatic asthma despite low-dose inhaled corticosteroid or non-corticosteroid asthma therapy. Patients aged 12 years and older who met the entry criteria including FEV1 40-85 percent of predicted normal, reversible bronchoconstriction of 15% with short-acting inhaled beta-agonist entered a 14-21 day run-in period. 270 patients (104 previously treated with inhaled corticosteroids) who met all the randomization criteria including asthma symptoms and rescue medication use were discontinued from asthma maintenance medication and randomized equally to treatment with QVAR REDIHALER 80 mcg/day, QVAR REDIHALER 160 mcg/day or placebo. Baseline FEV1 values were similar across treatments. The primary endpoint for this trial was the standardized baseline-adjusted trough morning forced expiratory volume in 1 second (FEV1) area under the effect curve from time zero to 12 weeks [FEV1 AUEC(0-12wk)]. Patients in both treatment groups had significantly greater improvements in trough FEV1 compared to placebo (QVAR REDIHALER 80 mcg/day, LS mean change of 0.124 L and QVAR REDIHALER 160 mcg/day, LS mean change of 0.116 L over 12 weeks) (Table 3).

In addition, the mean change from baseline is displayed in Figure 1. Both doses of QVAR REDIHALER were effective in improving asthma control with significantly greater improvements in FEV1 and morning PEF when compared to placebo. Reduction in asthma symptoms was also supportive of the efficacy of QVAR REDIHALER.

Figure 1: A 12‑Week Clinical Trial in Patients with Asthma: Mean Change in FEV1

Trial 2 (NCT02513160): This randomized, double-blind, parallel-group, placebo-controlled, 6-week, efficacy and safety trial compared QVAR REDIHALER 40 and 80 mcg given as 4 inhalations twice daily and placebo in adult and adolescent patients with persistent symptomatic asthma despite treatment with non-corticosteroid, inhaled corticosteroids (with or without a long acting beta agonist [LABA]), or combination asthma therapy. The study also included a reference treatment group, QVAR® Inhalation Aerosol (QVAR MDI) 40 mcg, 4 inhalations twice daily. Patients aged 12 years and older who met the entry criteria including FEV1 50-90% predicted normal, reversible bronchoconstriction of at least 10% with short-acting inhaled beta-agonist discontinued baseline asthma treatment and entered a 2-4 week run-in period. 425 patients (257 previously treated with ICS with or without LABA) who met all the randomization criteria including FEV1 of 40-85% predicted and 15% reversibility with short-acting inhaled beta-agonist, and asthma symptoms were randomized equally to QVAR REDIHALER 320 mcg/day, QVAR REDIHALER 640 mcg/day, QVAR MDI 320 mcg/day or placebo. Baseline FEV1 values were similar across treatments. The primary endpoint for this trial was the standardized baseline-adjusted trough morning forced expiratory volume in 1 second (FEV1) area under the effect curve from time zero to 6 weeks [FEV1 AUEC(0-6wk)]. Patients in both treatment groups had significantly greater improvements in trough FEV1 compared to placebo (QVAR REDIHALER 320 mcg/day, LS mean change of 0.144 L and QVAR REDIHALER 640 mcg/day, LS mean change of 0.150 L over 6 weeks) (Table 3). Treatment with QVAR MDI was similar. The change from baseline in morning FEV1 during the trial is displayed in Figure 2. Both doses of QVAR REDIHALER were effective in improving asthma control with significantly greater improvements in FEV1, morning PEF, weekly average of daily trough morning FEV1, reduced rescue medication use and improved asthma symptom scores than with placebo. Similar results were demonstrated with QVAR MDI.

Figure 2: A 6‑Week Dose Response Clinical Trial in Patients with Inhaled Corticosteroid-Dependent Asthma: Mean Change in FEV1 as Percent of Predicted

Side-by-side comparison of the primary analysis of standardized baseline-adjusted trough morning FEV1 from time zero to the end of the treatment period for both studies is shown below in Table 3.

Table 3: Primary Analysis of Standardized Baseline-Adjusted Trough Morning FEV1 (L) AUEC from Time Zero to the End of the Treatment Period 12-week Study and 6-week Dose Response Study

 | 12 weeks; FAS |  |  | 6 weeks; mITT Analysis set
Parameter; Statistic | Placebo (N=90) | QVAR REDIHALER 80 mcg/day (N=88) | QVAR REDIHALER 160 mcg/day (N=92) | Placebo (N=107) | QVAR REDIHALER 320 mcg/day (N=108) | QVAR REDIHALER 640 mcg/day (N=105) | QVAR MDI* 320 mcg/day (N=105)
Difference from placebo
Difference of Least Square mean | — | 0.124 | 0.116 | — | 0.144 | 0.150 | 0.148
95% CI | — | 0.054, 0.193 | 0.048, 0.185 | — | 0.0807, 0.2066 | 0.0868, 0.2132 | 0.0847, 0.2114

*QVAR MDI=QVAR Inhalation Aerosol

Pediatric Patients 4 to 11 Years of Age

This randomized, double-blind, parallel-group, placebo controlled, 12-week, global efficacy and safety trial (NCT02040766) compared QVAR REDIHALER 40 or 80 mcg, QVAR MDI 40 or 80 mcg or placebo given as 1 inhalation twice daily in pediatric patients aged 4 through 11 years old with persistent symptomatic asthma despite treatment with non-corticosteroid or low dose inhaled corticosteroid (with or without a long acting beta agonist [LABA]). Patients aged 4 to 5 years who were technically unable to complete spirometry participated in the safety population. Patients who met the entry criteria including FEV1 40-90% predicted normal and reversible bronchoconstriction of at least 12% with short acting inhaled beta agonist entered a 14-21 day run in period. Patients who met the randomization criteria including asthma symptoms and rescue medication use discontinued asthma therapy and were randomized equally across treatment groups. Five hundred sixty-eight (568) pediatric patients with symptomatic asthma of which 410 had previously been treated with low dose inhaled corticosteroids with or without a LABA were randomized to receive either 40 mcg or 80 mcg twice daily of QVAR REDIHALER, QVAR MDI or placebo. The primary endpoint was the change from baseline in trough percent predicted FEV1 AUEC (0-12 weeks). While the primary endpoint, was not statistically significant, change in weekly average of daily morning peak expiratory flow (PEF, L/min) over the 12 week treatment period was 11.3 [95% CI: 5.58, 17.06] and 8.5 [95% CI: 2.71, 14.24] for the 80 mcg/day and 160 mcg/day doses of QVAR REDIHALER, respectively, at nominal significance. Similar results were seen with evening PEF.

16 HOW SUPPLIED/STORAGE AND HANDLING

How Supplied

QVAR REDIHALER (beclomethasone dipropionate HFA) inhalation aerosol:

- 40 mcg is supplied in a box of one 10.6‑g canister containing 120 actuations which is enclosed within a sealed beige plastic actuator with a dose counter and hinged white cap, and Patient Information and Instructions for Use; box of one; 120 Actuations – NDC 59310-302-40

- 80 mcg is supplied in a box of one 10.6‑g canister containing 120 actuations which is enclosed within a sealed maroon plastic actuator with a dose counter and hinged white dust cap, and Patient Information and Instructions for Use; box of one; 120 Actuations – NDC 59310-304-80

The correct amount of medication in each inhalation cannot be assured after 120 actuations from the 10.6‑g canister even though the canister is not completely empty. Patients should be informed to discard the QVAR REDIHALER when the dose counter displays 0 or after the expiration date on the product, whichever comes first.

Storage and Handling

Store at 25ºC (77ºF).

Excursions between 15ºC and 30ºC (59ºF and 86ºF) are permitted (see USP Controlled Room Temperature). For optimal results, QVAR REDIHALER should be at room temperature when used.

Contents under pressure. Do not use or store near heat or open flame. Exposure to temperatures above 49ºC (120ºF) may cause bursting. Never throw QVAR REDIHALER into fire or incinerator.

Keep out of reach of children.

17 PATIENT COUNSELING INFORMATION

Advise the patient to read the FDA‑Approved Patient Labeling (Patient Information and Instructions for Use).

Patients should be given the following information:

Oropharyngeal Candidiasis

Inform patients that localized infections with Candida albicans occurred in the mouth and pharynx in some patients. If oropharyngeal candidiasis develops, treat it with appropriate local or systemic (i.e., oral) antifungal therapy while still continuing therapy with QVAR REDIHALER, but at times therapy with QVAR REDIHALER may need to be temporarily interrupted under close medical supervision. Rinsing the mouth with water without swallowing after inhalation is advised to help reduce the risk of thrush.

Status Asthmaticus and Acute Asthma Symptoms

Inform patients that QVAR REDIHALER is not a bronchodilator and is not intended for use as rescue medicine for acute asthma exacerbations. Advise patients to treat acute asthma symptoms with an inhaled, short‑acting beta2‑agonist such as albuterol. Instruct the patient to contact their physicians immediately if there is deterioration of their asthma.

Immunosuppression and Risk of Infections

Warn patients who are on immunosuppressant doses of corticosteroids to avoid exposure to chickenpox or measles and, if exposed, to consult their physicians without delay. Inform patients of potential worsening of existing tuberculosis; fungal, bacterial, viral, or parasitic infections; or ocular herpes simplex.

Hypercorticism and Adrenal Suppression

Advise patients that QVAR REDIHALER may cause systemic corticosteroid effects of hypercorticism and adrenal suppression. Additionally, instruct patients that deaths due to adrenal insufficiency have occurred during and after transfer from systemic corticosteroids. Patients should taper slowly from systemic corticosteroids if transferring to QVAR REDIHALER.

Immediate Hypersensitivity Reactions

Advise patients that immediate hypersensitivity reactions (e.g., urticaria, angioedema, rash, bronchospasm, and hypotension), including anaphylaxis, may occur after administration of QVAR REDIHALER. Patients should discontinue QVAR REDIHALER if such reactions occur and contact their healthcare provider or get emergency medical help.

Reduction in Bone Mineral Density

Advise patients who are at an increased risk for decreased BMD that the use of corticosteroids may pose an additional risk.

Reduced Growth Velocity

Inform patients that orally inhaled corticosteroids, including QVAR REDIHALER, may cause a reduction in growth velocity when administered to pediatric patients. Physicians should closely follow the growth of adolescents taking corticosteroids by any route.

Ocular Effects

Long-term use of inhaled corticosteroids may increase the risk of some eye problems (cataracts, glaucoma or blurred vision); consider regular eye examinations.

Pregnancy

Inform patients who are pregnant or nursing that they should contact their physician about the use of QVAR REDIHALER.

Use Daily for Best Effect

Patients should use QVAR REDIHALER at regular intervals as directed. Advise patients, if they miss a dose, to take their next dose at the same time they normally do. Individual patients will experience a variable time to onset and degree of symptom relief and the full benefit may not be achieved until treatment has been administered for 1 to 2 weeks or longer. Patients should not increase the prescribed dosage but should contact their physicians if symptoms do not improve or if the condition worsens. Instruct patients to not stop use of QVAR REDIHALER abruptly. Patients should contact their physicians immediately if they discontinue use of QVAR REDIHALER.

Caring for and Storing the Inhaler

Instruct patients to clean the mouthpiece of QVAR REDIHALER weekly with a clean, dry tissue or cloth. Instruct patients not to wash or put any part of QVAR REDIHALER in water. Patient should replace QVAR REDIHALER if washed or placed in water.

Instruct patients to store the inhaler at room temperature and to avoid exposure to extreme heat and cold.

Inform patients that shaking the inhaler prior to use is not necessary. Instruct patients not to shake the inhaler with the cap open to avoid possible actuation of the device.

Instruct patients to never take QVAR REDIHALER apart.

Inform patients that QVAR REDIHALER has a dose counter attached to the actuator at the rear of the mouth piece. When the patient receives the inhaler, the number 120 will be displayed. The dose counter will count down each time a spray is released. The dose-counter window displays the number of sprays left in the inhaler in units of two (e.g., 120, 118, 116, etc). When the counter displays 20, the color of the numbers will change to red to remind the patient to contact their pharmacist for a refill of medication or consult their healthcare provider for a prescription refill. When the dose counter reaches 0, the background will change to solid red. Inform patients to discard QVAR REDIHALER when the dose counter displays 0 or after the expiration date on the product, whichever comes first.

Manufactured for:

Teva Pharmaceuticals

Parsippany, NJ 07054

© 2025 Teva Respiratory, LLC

U.S. Patent 7,637,260; 8,132,712; 8,931,476

QVARH-004

Rev. 09/2025

PATIENT INFORMATION

QVAR REDIHALER® (kue' var red-ee-haye' ler)

(beclomethasone dipropionate HFA) inhalation aerosol

What is QVAR REDIHALER?

- QVAR REDIHALER is a breath‑actuated inhaled prescription medicine used as a maintenance treatment for the prevention and control of asthma in people 4 years of age and older.

- QVAR REDIHALER is not used to relieve sudden breathing problems.

It is not known if QVAR REDIHALER is safe and effective in children less than 4 years of age.

Who should not use QVAR REDIHALER?

Do not use QVAR REDIHALER:

- to treat sudden severe symptoms of asthma.

- as a rescue inhaler.

- if you are allergic to beclomethasone dipropionate or any of the ingredients in QVAR REDIHALER. See the end of this Patient Information leaflet for a complete list of ingredients in QVAR REDIHALER.

What should I tell my healthcare provider before using QVAR REDIHALER?

Before using QVAR REDIHALER, tell your healthcare provider about all of your medical conditions, including if you:

- are exposed to chickenpox or measles.

- have or have had tuberculosis (TB) or any untreated fungal, bacterial or viral infections, or eye infections caused by herpes.

- have weak bones (osteoporosis).

- have an immune system problem.

- have or have had eye problems, such as blurred vision, increased pressure in your eye (glaucoma) or cataracts.

- are pregnant or plan to become pregnant. It is not known if QVAR REDIHALER will harm your unborn baby.

- are breastfeeding or plan to breastfeed. It is not known if QVAR REDIHALER passes into your breast milk. Talk to your healthcare provider about the best way to feed your baby if you use QVAR REDIHALER.

Tell your healthcare provider about all of the medications you take, including prescription and over-the-counter medicines, vitamins, and herbal supplements.

How should I use QVAR REDIHALER?

Read the step-by-step Instructions for Use for QVAR REDIHALER at the end of this Patient Information leaflet.

- Use QVAR REDIHALER exactly as your healthcare provider tells you to. Do not use QVAR REDIHALER more often than it is prescribed.
- Do not shake the inhaler before using it. Especially, do not shake the inhaler with the cap open. This could cause the device to accidentally release medicine before you are ready to take it.
- Do not prime QVAR REDIHALER. The inhaler does not need to be primed.
- If your child needs to use QVAR REDIHALER, watch your child closely to make sure your child uses the inhaler correctly.
- Do not change or stop using QVAR REDIHALER or other asthma medicines used to treat your breathing problems unless your healthcare provider tells you to. Your healthcare provider will change your medicines as needed.
- You must use QVAR REDIHALER regularly. It may take 2 to 4 weeks, or longer, after you start using QVAR REDIHALER for your asthma symptoms to get better. Do not stop using QVAR REDIHALER, even if you are feeling better, unless your healthcare provider tells you to.
- QVAR REDIHALER comes in 2 strengths (40 mcg and 80 mcg). Your healthcare provider has prescribed the strength that is best for you. Pay attention to the differences between QVAR REDIHALER and your other inhaled medicines, including their prescribed use and the way they look.
- QVAR REDIHALER does not relieve sudden asthma symptoms. Always have a rescue inhaler with you to treat sudden symptoms. Use your rescue inhaler if you have breathing problems between doses of QVAR REDIHALER. If you do not have a rescue inhaler, call your healthcare provider to have a rescue inhaler prescribed for you.
- Rinse your mouth with water without swallowing after each dose of QVAR REDIHALER. This will help lessen the chance of getting a yeast infection (thrush) in your mouth and throat.
- Do not spray QVAR REDIHALER in your face or eyes. If you accidentally get QVAR REDIHALER in your eyes, rinse your eyes with water and if redness or irritation continues, call your healthcare provider.

What should I avoid while using QVAR REDIHALER?

If you have not had, or have not been vaccinated against, chickenpox or measles, you should stay away from people who are infected.

What are the possible side effects of QVAR REDIHALER?

QVAR REDIHALER may cause serious side effects, including:

- fungal infections (thrush) in your mouth and throat. You may develop a yeast infection (Candida albicans) in your mouth and throat. Tell your healthcare provider if you have any redness or white colored patches in your mouth or throat. Rinse your mouth with water without swallowing after using QVAR REDIHALER to help prevent an infection in your mouth or throat.

- worsening asthma or sudden asthma attacks. You should contact your healthcare provider right away if you do not get relief from your sudden asthma attacks, after using your rescue inhaler, during your treatment with QVAR REDIHALER.

- reduced adrenal function (adrenal insufficiency). Reduced adrenal function that can lead to death can happen when you stop taking oral corticosteroid medicines and start using inhaled corticosteroid medicines. Reduced adrenal function can also happen in people who take higher doses of QVAR REDIHALER than recommended over a long period of time. When your body is under stress such as from fever, trauma (such as a car accident), infection, or surgery, reduced adrenal function can get worse. Signs and symptoms of reduced adrenal function may include:

○ feeling tired or exhausted (fatigue) ○ lack of energy ○ low blood pressure (hypotension)

○ dizziness or feeling faint ○ nausea and vomiting ○ weakness

- immune system effects and a higher chance for infections. Tell your healthcare provider about any signs or symptoms of infection such as:

○ fever ○ chills ○ pain ○ feeling tired

○ body aches ○ nausea ○ vomiting

- increased wheezing (bronchospasm) right after using QVAR REDIHALER. Always have a rescue inhaler with you to treat sudden wheezing.

- serious allergic reactions. Stop using QVAR REDIHALER and call your healthcare provider or get emergency medical help right away if you get any of the following signs or symptoms of a serious allergic reaction:

○ hives ○ swelling of your lips, tongue or face ○ rash ○ breathing problems

- slowed growth in children. Children should have their growth checked regularly while using QVAR REDIHALER.

- lower bone density. This may be a problem for people who already have a higher chance for low bone density (osteoporosis).

- eye problems. If you have had glaucoma, cataracts or blurred vision in the past, you should have regular eye exams while using QVAR REDIHALER.

The most common side effects of QVAR REDIHALER include:

- yeast infection in the mouth (oral candidiasis)
- cold symptoms (upper respiratory tract infection)
- pain in the throat (oropharyngeal pain)
- pain or swelling in your nose and throat (nasopharyngitis)
- sinus irritation (sinusitis)
- hay fever (allergic rhinitis)

Tell your healthcare provider if you have any side effect that bothers you or that does not go away.

These are not all the possible side effects of QVAR REDIHALER. Ask your healthcare provider or pharmacist for more information.

Call your doctor for medical advice about side effects. You may report side effects to FDA at 1-800-FDA-1088.

How should I store QVAR REDIHALER?

- Store QVAR REDIHALER at room temperature between 68ºF to 77ºF (20ºC to 25ºC). Avoid exposure to extreme heat or cold.
- Keep the white cap on the inhaler closed during storage.
- Keep your QVAR REDIHALER inhaler dry and clean at all times.
- Clean the mouthpiece of your QVAR REDIHALER weekly with a clean, dry tissue or cloth.
- Your QVAR REDIHALER canister should only be used with the QVAR REDIHALER actuator. Do not use any other medicines in your QVAR REDIHALER actuator.
- The contents of your QVAR REDIHALER canister are under pressure. Do not puncture the QVAR REDIHALER canister.
- Do not take QVAR REDIHALER apart.
- If you drop your QVAR REDIHALER, inspect it for damage before use. If the QVAR REDIHALER is damaged, do not use the damaged QVAR REDIHALER. Call your healthcare provider or pharmacist to replace the QVAR REDIHALER.
- Do not store your QVAR REDIHALER canister near heat or a flame. Temperatures above 120ºF (49°C) may cause the canister to burst.
- Do not throw your QVAR REDIHALER canister into a fire or incinerator.

Keep QVAR REDIHALER and all medicines out of the reach of children.

General information about the safe and effective use of QVAR REDIHALER.

Medicines are sometimes prescribed for purposes other than those listed in a Patient Information leaflet. Do not use QVAR REDIHALER for a condition for which it was not prescribed. Do not give QVAR REDIHALER to other people, even if they have the same symptoms that you have. It may harm them. You can ask your pharmacist or healthcare provider for information about QVAR REDIHALER that is written for health professionals.

What are the ingredients in QVAR REDIHALER?

Active ingredient: beclomethasone dipropionate.

Inactive ingredients: propellant HFA-134a and ethanol.

Manufactured for:

Teva Pharmaceuticals

Parsippany, NJ 07054

© 2025 Teva Respiratory, LLC.

For more information, go to www.QVAR.com or call 1-888-483-8279.

This Patient Information has been approved by the U.S. Food and Drug Administration. Revised: 09/2025

INSTRUCTIONS FOR USE

QVAR REDIHALER® (kue' var red-ee-haye’ ler)

(beclomethasone dipropionate HFA)

inhalation aerosol

Your QVAR REDIHALER Inhaler

Overview

When you are ready to use your QVAR REDIHALER for the first time, remove the inhaler from the carton.

Important information:

- There is no button. You must close the white cap to prepare the inhaler with medicine before each inhalation.
- Do not shake. This breath-actuated device does not need to be shaken. This is not a press-and-breathe inhaler.
- Do not prime QVAR REDIHALER. The inhaler does not need to be primed.
- Do not use a spacer or volume holding chamber with QVAR REDIHALER.
- Always use the inhaler in the upright position (with the mouthpiece down).
- After the inhaler is prepared, it will deliver 1 inhalation of medicine when you breathe in (inhale) through the mouthpiece. Your dose might require more than 1 inhalation.
- Do not open the white cap or leave it open unless you are ready for your next inhalation. If the cap has been opened for more than 2 minutes or left in the open position, you will need to close the white cap before use.
- Do not breathe out or blow into any part of the inhaler. Breathing out or blowing into the inhaler can damage it.
- Do not suddenly stop using your QVAR REDIHALER. Contact your healthcare provider immediately if you stop using your QVAR REDIHALER.

There are 2 main parts of your QVAR REDIHALER including:

- the inhaler body with the mouthpiece. See Figure A.

- the white cap that covers the mouthpiece of the inhaler. See Figure A.

Figure A

About the Dose Counter

There is a dose counter in the back of the inhaler with a viewing window that shows you how many inhalations of medicine you have left. See Figure B.

- Your QVAR REDIHALER contains 120 inhalations. See Figure B.

- The counter on the back of your inhaler shows how many inhalations you have left. When there are 20 inhalations left, the numbers in the dose counter will change to red and you should refill your prescription or ask your healthcare provider for another prescription.

- When the dose counter shows ‘0’, the background will turn solid red and your inhaler is empty. You should stop using the inhaler and throw it away. Do not put your inhaler into a fire or incinerator. See Figure B.

Figure B

Important:

- The white cap must be closed to prepare the inhaler before each inhalation or you will not receive your medicine. See Figure C.

- If the white cap is open, close the white cap to prepare your inhaler and look at the dose counter window to make sure that your inhaler is not empty. See Figure B.

- Do not open the cap until you are ready to take your inhalation.

Figure C

Using your QVAR REDIHALER:

Step 1. Open the white cap

- Open the white cap. See Figure D.

- Breathe out fully, away from the inhaler. Do not blow into the inhaler.

Figure D

Remember:

- Do not open the cap until you are ready to take your inhalation.

- Never breathe out or blow into the inhaler. Breathing out or blowing into the inhaler can damage it.

Step 2. Inhale 1 Time

- Place the mouthpiece in your mouth and close your lips around it so you form a good seal.

- Inhale deeply to release the medicine.

- Remove the inhaler and hold your breath for 5 to 10 seconds, then breathe out slowly, away from the inhaler.

Figure E

Remember:

- Hold the inhaler upright as you take your inhalation. See Figure E.

Step 3. Close the white cap

- Close the white cap after inhaling to prepare your next inhalation. See Figure F.

Figure F

If your healthcare provider has told you to take more than 1 inhalation per dose, make sure the white cap is closed and repeat Step 1 to Step 3.

After taking your prescribed number of inhalations, rinse your mouth with water without swallowing to help reduce the risk of a fungal infection (thrush) in your mouth.

How to store your QVAR REDIHALER

- Store QVAR REDIHALER at room temperature between 68ºF to 77ºF (20ºC to 25ºC). Avoid exposure to extreme heat or cold.

- Keep the white cap on the inhaler closed during storage.

- Keep your QVAR REDIHALER inhaler dry and clean at all times.

- If you drop your QVAR REDIHALER, inspect it for damage before use. If the QVAR REDIHALER is damaged, do not use the damaged QVAR REDIHALER. Call your doctor or pharmacist to replace the QVAR REDIHALER.

- Do not use or store your QVAR REDIHALER near heat or open flame. Exposure to temperatures above 120ºF (49ºC) may cause the canister to burst.

- Do not throw QVAR REDIHALER into fire or an incinerator.

- Throw away QVAR REDIHALER when the dose counter displays ‘0,’ or after the expiration date on the package, whichever comes first.

- Keep your QVAR REDIHALER and all medicines out of the reach of children.

Cleaning your QVAR REDIHALER

- Do not wash or put any part of your QVAR REDIHALER in water.

- Clean the mouthpiece of your QVAR REDIHALER weekly with a clean, dry tissue or cloth.

Support

- If you have any questions about QVAR REDIHALER or how to use your inhaler, go to www.QVAR.com or call 1-888-483-8279.

This Instructions for Use has been approved by the U.S. Food and Drug Administration.

Manufactured for:

Teva Pharmaceuticals

Parsippany, NJ 07054

© 2025 Teva Respiratory, LLC.

QVARHIFU-004

Rev. 09/2025

40 mcg Package/Label Display Panel Part 2 of 2

QVAR Redihaler® (beclomethasone dipropionate HFA) 40 mcg, 120 Metered Inhalations Carton Text

NDC 59310-302-40

QVAR

RediHaler

(beclomethasone dipropionate HFA)

Breath-Actuated Inhalation Aerosol

40 mcg

For oral inhalation only

Lift side flap

for instructions on

how to use inhaler

120

Metered

Inhalations

10.6g NET CONTENTS

80 mcg Package/Label Display Panel Part 2 of 2

QVAR RediHaler® (beclomethasone dipropionate HFA) 80 mcg, 120 Metered Inhalations Carton Text

NDC 59310-304-80

QVAR

RediHaler

(beclomethasone dipropionate HFA)

Breath-Actuated Inhalation Aerosol

80 mcg

For oral inhalation only

Lift side flap

for instructions on

how to use inhaler

120

Metered

Inhalations

10.6g NET CONTENTS